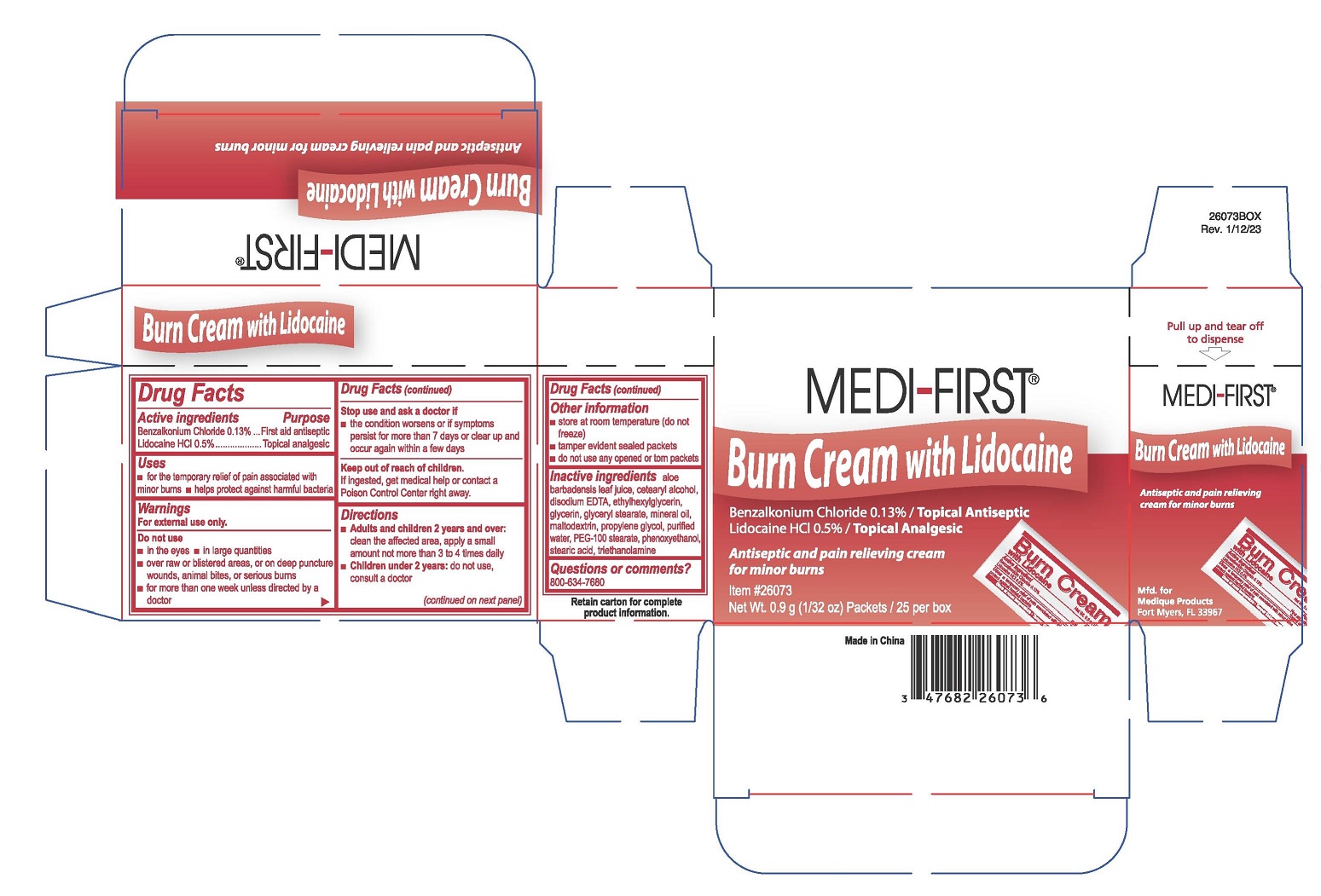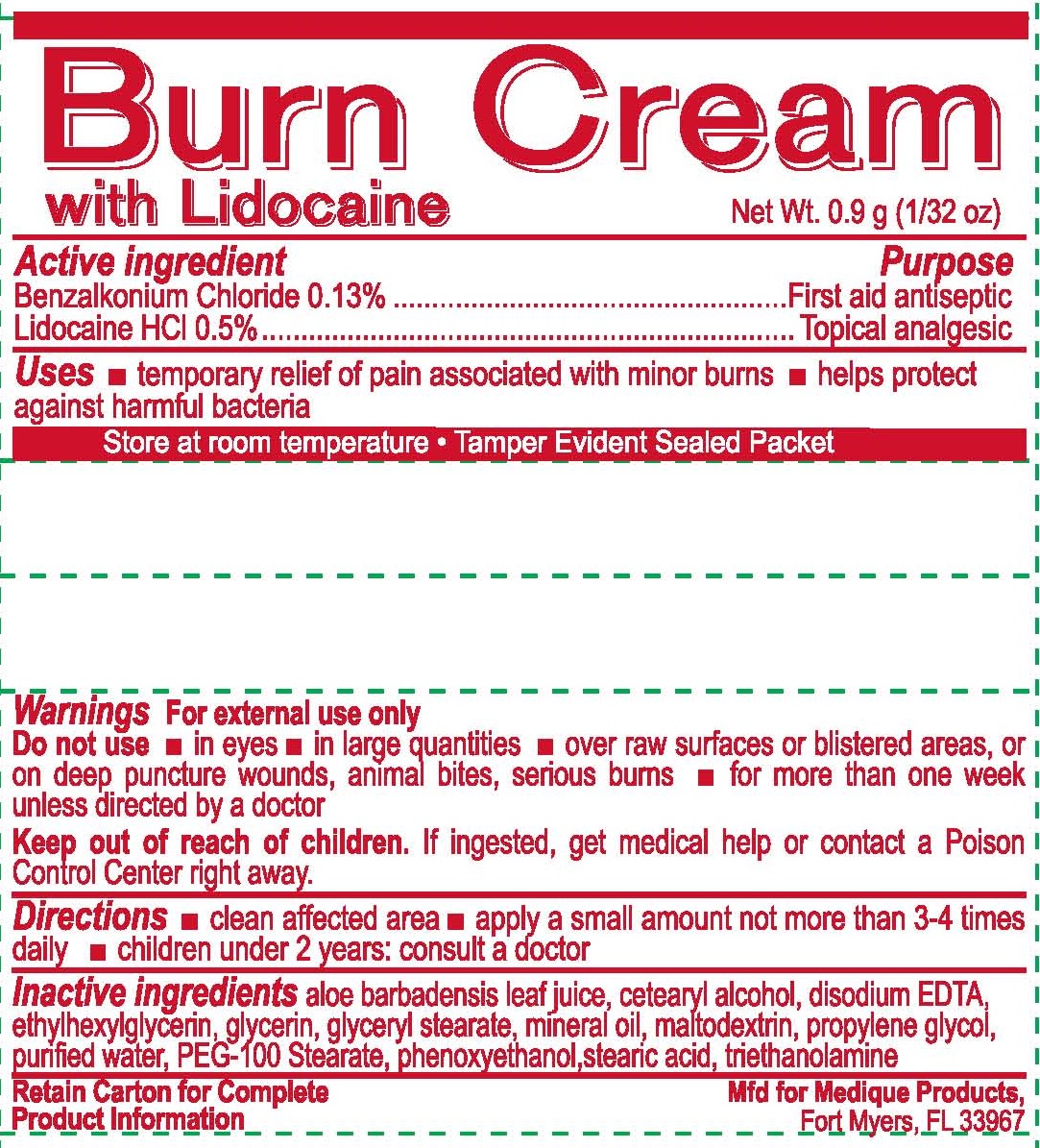 DRUG LABEL: MEDI-FIRST
NDC: 71927-019 | Form: CREAM
Manufacturer: Orazen Inc
Category: otc | Type: HUMAN OTC DRUG LABEL
Date: 20250903

ACTIVE INGREDIENTS: LIDOCAINE HYDROCHLORIDE 5 mg/1 g; BENZALKONIUM CHLORIDE 1.3 mg/1 g
INACTIVE INGREDIENTS: ETHYLHEXYLGLYCERIN; MALTODEXTRIN; ALOE VERA LEAF; GLYCERYL MONOSTEARATE; WATER; GLYCERIN; MINERAL OIL; PEG-100 STEARATE; PHENOXYETHANOL; PROPYLENE GLYCOL; TROLAMINE; STEARIC ACID; CETOSTEARYL ALCOHOL; EDETATE DISODIUM ANHYDROUS

71927-019-01, -02 MEDI-FIRST
Burn cream with Lidocaine

Active ingredients

Benzalkonium Chloride 0.13%

Lidocaine HCI 0.5%

Purpose

First aid antiseptic

Topical analgesic

Uses

- for the temporary relief of pain associated with minor burns
- helps protect against harmful bacteria

Warnings

For external use only.

Do not use

- in the eyes
- in large quantities
- over raw or blistered areas, or on deep puncture wounds, animal bites, or serious burns
- for more than one week unless directed by a doctor

Stop use and ask a doctor if

- the condition worsens or if symptoms persist for more than 7 days or clear up and occur again within a few days

Keep out of reach of children.

If ingested, get medical help or contact a Poison Control Center right away.

Directions

- Adults and children 2 years and over:clean the affected area, apply a small amount not more than 3 to 4 times daily
- Children under 2 years:do not use, consult a doctor

Other information

- store at room temperature (do not freeze)
- tamper evident sealed packets
- do not use any opened or torn packets

Inactive ingredients

aloe barbadensis leaf juice, cetearyl alcohol,disodium EDTA, ethylhexylglycerin, glycerin, glyceryl stearate, mineral oil, maltodextrin, propylene glycol, purified water, PEG-100 stearate,phenoxyethanol, stearic acid, triethanolamine

Questions or comments?

800-634-7680